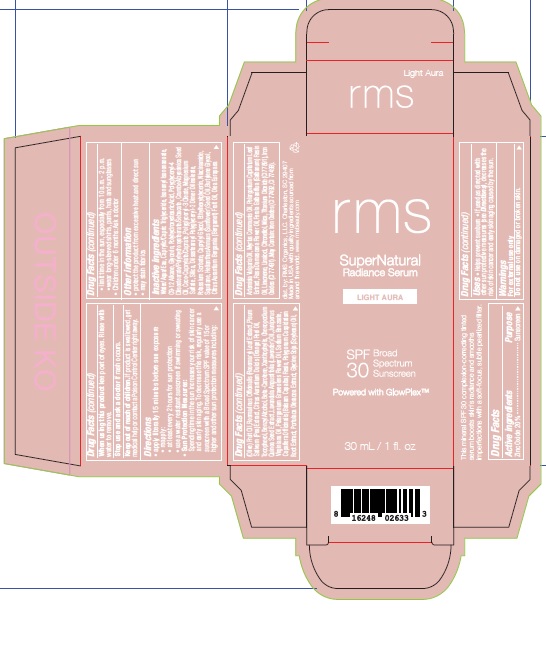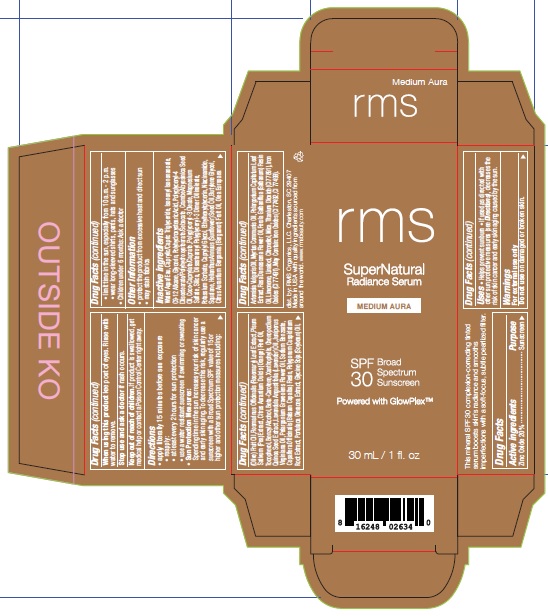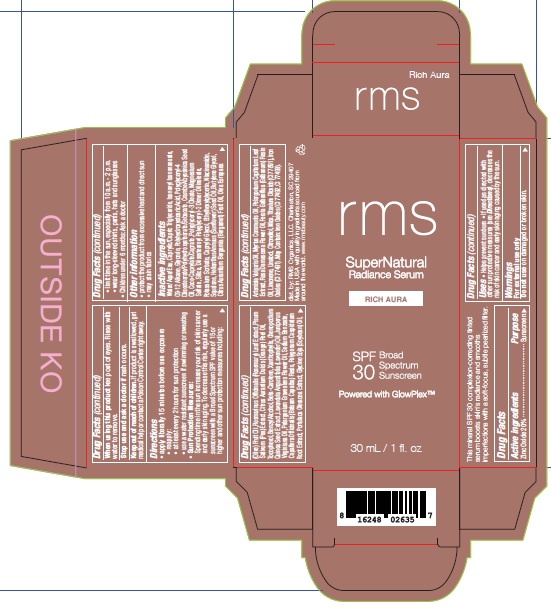 DRUG LABEL: RMS SUPERNATURAL RADIANCE SERUM SPF 30 SUNSCREEN MEDIUM AURA
NDC: 83249-002 | Form: EMULSION
Manufacturer: Rms organics LLC
Category: otc | Type: HUMAN OTC DRUG LABEL
Date: 20241009

ACTIVE INGREDIENTS: ZINC OXIDE 200 mg/1 mL
INACTIVE INGREDIENTS: MEDIUM-CHAIN TRIGLYCERIDES; ISONONYL ISONONANOATE; GLYCERIN; DIISOSTEAROYL POLYGLYCERYL-3 DIMER DILINOLEATE; POTASSIUM SORBATE; WATER; PURSLANE; SOYBEAN OIL; LAVENDER OIL; OLIVE OIL; CHENOPODIUM QUINOA SEED; PELARGONIUM GRAVEOLENS FLOWER OIL; SODIUM BENZOATE; SUNFLOWER OIL; BUTYLENE GLYCOL; BERGAMOT OIL; PEA; LUTEIN; JUNIPERUS VIRGINIANA OIL; COPAIFERA OFFICINALIS RESIN; POLYGONUM CUSPIDATUM ROOT; ARTEMISIA VULGARIS TOP OIL; MAGNESIUM SULFATE, UNSPECIFIED; CAPRYLYL GLYCOL; NIACINAMIDE; SQUALANE; MICA; TITANIUM DIOXIDE; FERRIC OXIDE RED; FERROSOFERRIC OXIDE; MYRTLE LEAF OIL; PELARGONIUM CAPITATUM LEAF; ROSA DAMASCENA FLOWER OIL; LIMONENE, (+)-; LINALOOL, (+)-; .BETA.-CITRONELLOL, (R)-; FERRIC OXIDE YELLOW; POLYGLYCERYL-4 DIISOSTEARATE/POLYHYDROXYSTEARATE/SEBACATE; COCO-CAPRYLATE/CAPRATE; POLYGLYCERYL-3 OLEATE; BETA CAROTENE; ORANGE OIL; GALBANUM OIL; ROSEMARY; TOCOPHEROL; BENZYL ALCOHOL; POLYHYDROXYSTEARIC ACID (2300 MW); CRAMBE HISPANICA SUBSP. ABYSSINICA SEED OIL; SILICON DIOXIDE; ETHYLHEXYLGLYCERIN

RMS SUPERNATURAL RADIANCE SERUM SPF 30 SUNSCREEN

Active ingredients

Zinc Oxide 20%

Purpose

Sunscreen

Uses

- Helps prevent sunburn
- If used as directed with other sun protective measures (see Directions), decreases the risk of skin cancer and early skin aging caused by the sun.

Warnings

For external use only

Do not use

on damaged or broken skin.

When using this product

keep out of eyes. Rinse with water to remove.

Stop use and ask a doctor

if rash occurs.

Keep out of reach of children.

If product is swallowed, get medical help or contact a Poison Control Center right away.

Directions

- apply liberally 15 minutes before sun exposure
- reapply:
- at least every 2 hours for sun protection
- use a water resistant suncreen if swimming or sweating
- Sun Protection Measures: Spending time in the sun increases your risk of skin cancer and early skin aging. To decrease this risk, regularly use a sunscreen with a Broad Spectrum SPF value of 15 or higher and other sun protection measures including:
- limit tine in the sun, especially from 10 a.m. - 2 p.m.
- wear long-sleeved shirts, pants, hats and sunglasses
- Children under 6 months: Ask a doctor

Other information

- protect the product from excessive heat and direct sun
- may stain fabrics

Inactive ingredients

Water/Aqua/Eau, Caprylic/Capric Triglyceride, Isononyl Isononanoate, C9-12 Alkane, Glycerin, Polyhydroxystearic Acid, Polyglyceryl-4 Diisostearate/Polyhydroxystearate/Sebacate, Crambe Abyssinica Seed Oil, Coco-Caprylate/Caprate, Polyglyceryl-3 Oleate, Magnesium Sulfate, Silica, Diisostearoyl Polyglyceryl-3 Dimer Dilinoleate, Potassium Sorbate, Caprylyl Glycol, Ethylhexylglycerin, Niacinamide, Squalane, Helianthus Annuus (Sunflower) Seed Oil, Butylene Glycol, Citrus Aurantium Bergamia (Bergamot) Fruit Oil, Olea Europaea Olive) Fruit Oil, Rosmarinus Officinalis (Rosemary) Leaf Extract, Pisum Sativum (Pea) Extract, Citrus Aurantium Dulcis (Orange) Peel Oil, Tocopherol, Benzyl Alcohol, Beta-Carotene, Xanthophylls, Chenopodium Quinoa Seed Extract, Lavandula Angustifolia (Lavender) Oil, Juniperus Virginiana Oil, Pelargonium Graveolens Flower Oil, Sodium Benzoate, Copaifera Officinalis (Balsam Copaiba) Resin, Polygonum Cuspidatum Root Extract, Portulaca Oleracea Extract, Glycine Soja (Soybean) Oil, Artemisia Vulgaris Oil, Myrtus Communis Oil, Pelargonium Capitatum Leaf Extract, Rosa Damascena Flower Oil, Ferula Galbaniflua (Galbanum) Resin Oil, Limonene, Linalool, Citronellol, Mica, Titanium Dioxide (CI 77891), Iron Oxides (CI 77491). May Contain: Iron Oxides (CI 77492, CI 77499).

Company Informataion

dist. by: RMS Organics, LLC. Charleston, SC 29407
Made in USA with quality ingredients sourced from around the world.

www.rmsbeauty.com